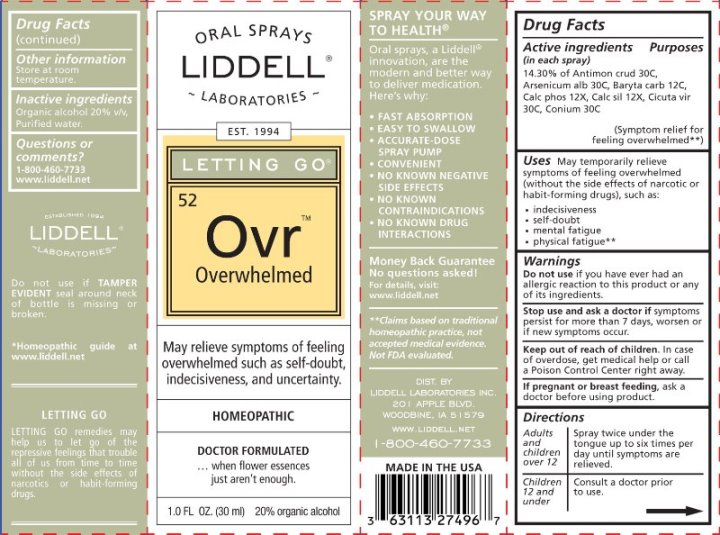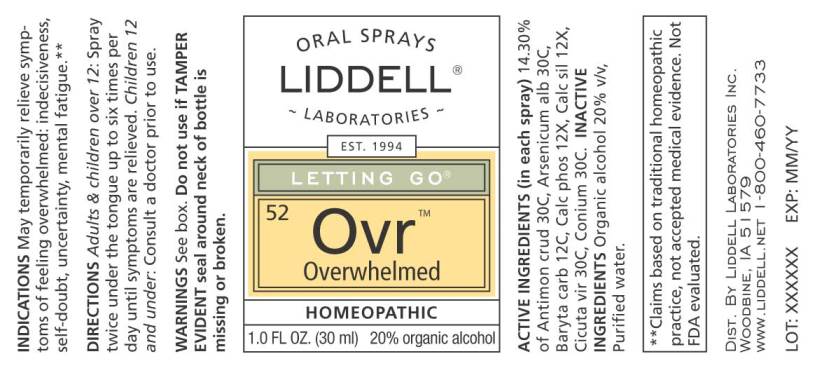 DRUG LABEL: Overwhelmed
NDC: 50845-0268 | Form: SPRAY
Manufacturer: Liddell Laboratories
Category: homeopathic | Type: HUMAN OTC DRUG LABEL
Date: 20241104

ACTIVE INGREDIENTS: ACONITUM NAPELLUS WHOLE 30 [hp_C]/1 mL; SEMECARPUS ANACARDIUM JUICE 30 [hp_C]/1 mL; ANTIMONY TRISULFIDE 30 [hp_C]/1 mL; BARIUM CARBONATE 12 [hp_C]/1 mL; TRIBASIC CALCIUM PHOSPHATE 12 [hp_X]/1 mL; CALCIUM SILICATE 12 [hp_X]/1 mL; CICUTA VIROSA ROOT 30 [hp_C]/1 mL; CONIUM MACULATUM FLOWERING TOP 30 [hp_C]/1 mL
INACTIVE INGREDIENTS: WATER; ALCOHOL

DRUG FACTS:

ACTIVE INGREDIENTS:

(in each spray) 12.50% of Aconitum Napellus 30C, Anacardium Orientale 30C, Antimonium Crudum 30C, Baryta Carbonica 12C, Calcarea Phosphorica 12X, Calcarea Silicata 12X, Cicuta Virosa 30C, Conium Maculatum 30C.

INDICATIONS:

May temporarily relieve symptoms of feeling overwhelmed (without the side effects of narcotic or habit forming drugs), such as:

• indecisiveness
• self-doubt
• mental fatigue
• physical fatigue**
**Claims based on traditional homeopathic practice, not accepted medical evidence. Not FDA evaluated.

WARNINGS:

Do not use if you have ever had an allergic reaction to this product or any of its ingredients.

Stop use and ask a doctor if symptoms persist for more than 7 days, worsen, or if new symptoms occur.

Keep out of reach of children. In case of overdose, get medical help or call a Poison Control Center right away.

If pregnant or breast feeding, ask a doctor before using product.

Do not use if TAMPER EVIDENT seal around neck of bottle is missing or broken.

Other information Store at room temperature.

Keep out of reach of children. In case of overdose, get medical help or call a Poison Control Center right away.

DIRECTIONS:

Adults and children over 12 Spray twice under the tongue up to six times per day until symptoms are relieved.

Children 12 and under Consult a doctor prior to use.

INDICATIONS:

May temporarily relieve symptoms of feeling overwhelmed (without the side effects of narcotic or habit forming drugs), such as:

• indecisiveness
• self-doubt
• mental fatigue
• physical fatigue**
**Claims based on traditional homeopathic practice, not accepted medical evidence. Not FDA evaluated.

INACTIVE INGREDIENTS:

Organic alcohol 20% v/v, Purified water.

QUESTIONS:

DIST. BY

LIDDELL LABORATORIES, INC.

201 APPLE BLVD.

WOODBINE, IA 51579

WWW.LIDDELL.NET

1-800-460-7733

PACKAGE LABEL DISPLAY:

ORAL SPRAYS
LIDDELL
LABORATORIES

EST 1994
LETTING GO

52Ovr
Overwhelmed

May relieve symptoms of feeling
overwhelmed such as self-doubt,
indecisiveness, and uncertainty.

HOMEOPATHIC

DOCTOR FORMULATED
...when flower essences just aren't enough.

1.0 FL OZ. (30 ml)